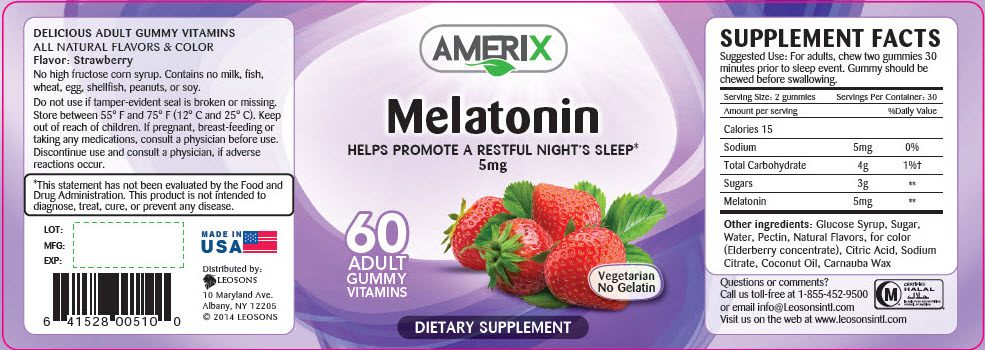 DRUG LABEL: Amerix Melatonin
NDC: 69626-0510 | Form: TABLET, CHEWABLE
Manufacturer: Leosons Overseas Corp
Category: other | Type: DIETARY SUPPLEMENT
Date: 20180914

ACTIVE INGREDIENTS: Melatonin 2.5 mg/1 1
INACTIVE INGREDIENTS: Corn Syrup; sucrose; water; Pectin; Citric Acid Monohydrate; Sodium Citrate, Unspecified Form; Coconut Oil; Carnauba Wax

AMERIX Melatonin

STATEMENT OF IDENTITY

SUPPLEMENT FACTS
Suggested Use: For adults, chew two gummies 30 minutes prior to sleep event. Gummy should be chewed before swallowing.
Serving Size: 2 gummies | Servings Per Container: 30
Amount per serving | %Daily Value
Calories 15
Sodium | 5mg | 0%
Total Carbohydrate | 4g | 1%†
Sugars | 3g | **
Melatonin | 5mg | **

Other ingredients: Glucose Syrup, Sugar, Water, Pectin, Natural Flavors, for color (Elderberry concentrate), Citric Acid, Sodium Citrate, Coconut Oil, Carnauba Wax

HEALTH CLAIM

DELICIOUS ADULT GUMMY VITAMINS

ALL NATURAL FLAVORS & COLOR

Flavor: Strawberry

No high fructose corn syrup. Contains no milk, fish, wheat, egg, shellfish, peanuts, or soy.

Do not use if tamper-evident seal is broken or missing. Store between 55° F and 75° F (12° C and 25° C). Keep out of reach of children. If pregnant, breast-feeding or taking any medications, consult a physician before use. Discontinue use and consult a physician, if adverse reactions occur.

HEALTH CLAIM

*This statement has not been evaluated by the Food and Drug Administration. This product is not intended to diagnose, treat, cure, or prevent any disease.

Questions or comments?

Call us toll-free at 1-855-452-9500 or email info@Leosonsintl.com

Visit us on the web at www.leosonsintl.com

HEALTH CLAIM

CERTIFIED
HALAL
ISLAMIC FOOD AND NUTRITION
COUNCIL OF AMERICA

HEALTH CLAIM

LOT:

MFG:

EXP:

MADE IN USA

HEALTH CLAIM

Distributed by:
LEOSONS
10 Maryland Ave.
Albany, NY 12205
© 2014 LEOSONS

PRINCIPAL DISPLAY PANEL - 60 Vitamin Bottle Label

AMERIX

Melatonin

HELPS PROMOTE A RESTFUL NIGHT'S SLEEP*
5mg

60
ADULT
GUMMY
VITAMINS

Vegetarian
No Gelatin

DIETARY SUPPLEMENT